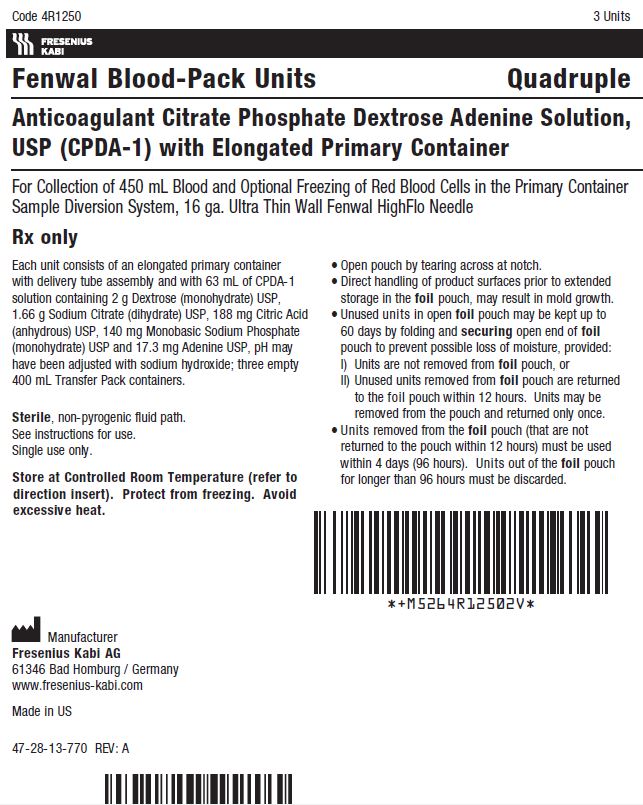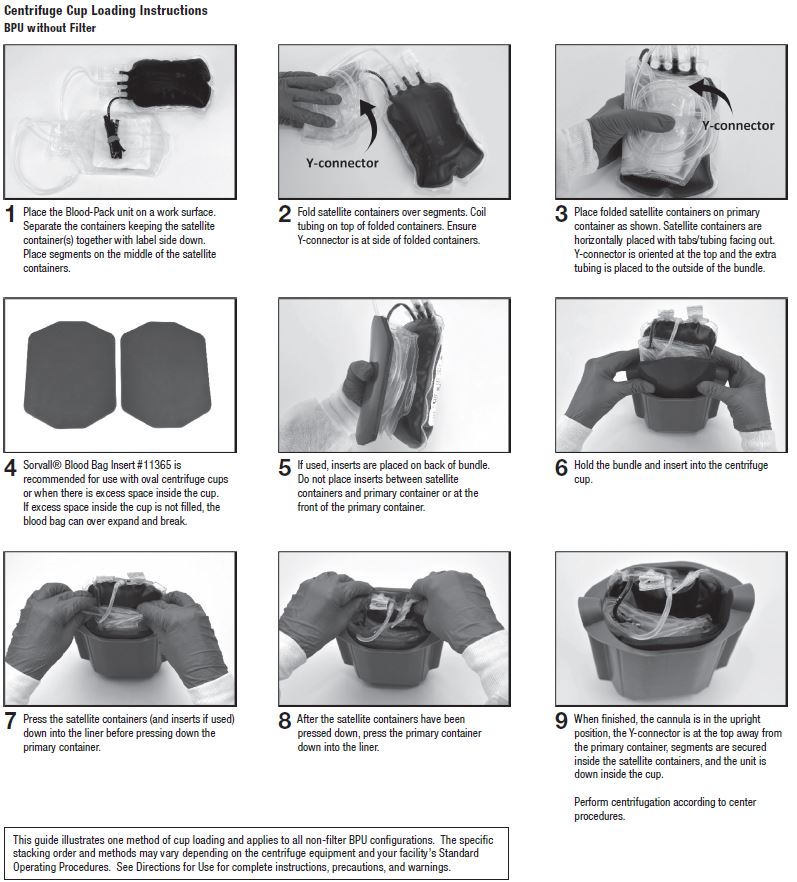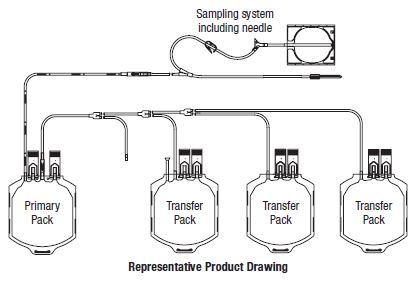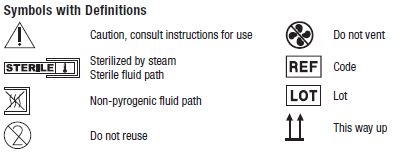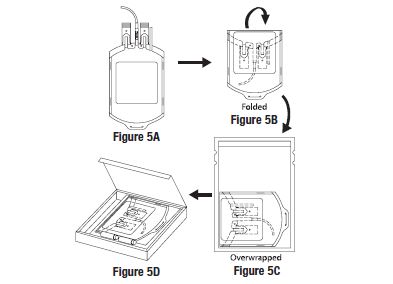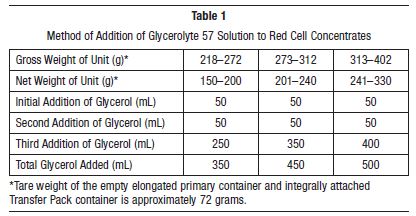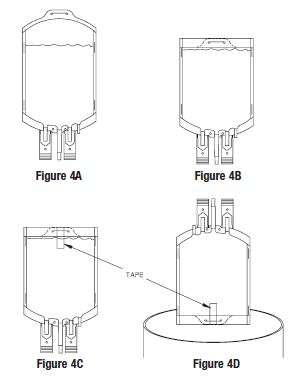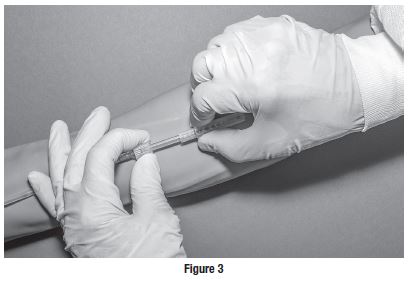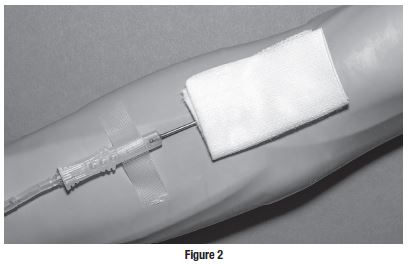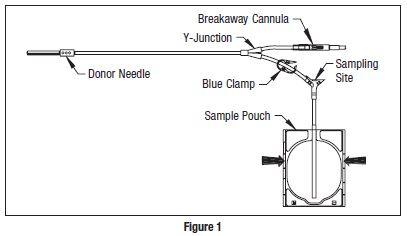 DRUG LABEL: CPDA-1
NDC: 0942-6322 | Form: SOLUTION
Manufacturer: Fenwal, Inc.
Category: prescription | Type: HUMAN PRESCRIPTION DRUG LABEL
Date: 20191119

ACTIVE INGREDIENTS: Dextrose Monohydrate 2 g/63 mL; Trisodium Citrate Dihydrate 1.66 g/63 mL; Anhydrous Citric Acid 188 mg/63 mL; Sodium Phosphate, Monobasic, Monohydrate 140 mg/63 mL; Adenine 17.3 mg/63 mL
INACTIVE INGREDIENTS: Sodium Hydroxide

4R1250 Fresenius Kabi Fenwal Blood-Pack Units Rx only Using Anticoagulant Citrate Phosphate Dextrose Adenine Solution, USP (CPDA-1) with Elongated Primary Container and the Fenwal HighFlo Needle

Contains Sample Diversion System for the collection of unanticoagulated whole blood samples for laboratory testing.

The elongated primary container may be used to collect and store 450 mL of blood for 35 (CPDA-1) days. It may also be used to prepare and store frozen red cells using the high glycerol (40% W/V) technique.

Instructions for Use

Collection Procedure:

Use aseptic technique.

Notes:

• If Sample Diversion System is not used, donor samples may be collected using an alternate method following standard procedures.
• Nominal tubing dimensions of product are 0.118" inner diameter x 0.025" wall thickness.

Precautions:

• Upon removal of Blood-Pack unit from the clear plastic overwrap, visually inspect the unit.
• Do not use the product if the in-line cannula is broken and/or anticoagulant is present in the sample pouch or in the tubing from the in-line cannula to the sample pouch and HighFlo1 needle (see Figure 1). Note that condensation in the empty tubing of the Blood-Pack unit is expected as a result of the sterilization process.
• Do not use unless the solutions are clear.
• Since plastics become brittle at freezer temperatures, use caution during handling to prevent container breakage.
• The elongated primary container should not be used for the storage of red cells at liquid nitrogen temperatures.

1. Identify Blood-Pack unit using appropriate donor identification system.

2. Adjust donor scale to desired collection weight.

3. Position primary container on the donor scale as far as possible below donor arm.

4. Clamp donor tubing between the needle and Y-junction. (This step can be performed prior to step 1 or 2.)

5. Visually inspect the tubing from the in-line cannula to the sample pouch and donor needle, as well as the sample pouch to reconfirm that there is no anticoagulant present.

Note: Ensure that the sample pouch remains below the donor’s arm.

6. Following blood center procedures, apply pressure to donor’s arm and disinfect site of venipuncture.

7. Remove needle cover per instructions below:

a) Holding the hub and cover near the tamper-evident seal, twist cover and hub in opposite directions to break seal.
b) Remove needle cover, being careful not to drag the cover across the needle point.

8. Following blood center procedures, perform venipuncture, appropriately secure donor needle and/or tubing and release clamp on donor tubing.

9. When good blood flow is established, stabilize the front of the needle guard to arm with tape (see Figure 2).

10. Allow the sample pouch to fill with blood according to center procedure. Monitor blood flow into sample pouch.

Notes:

• The sample pouch contains an average fill volume of approximately 53 mL with a maximum fill volume of approximately 60 mL when filled to capacity.
• If less blood sample volume is required, the flow to the sample pouch may be stopped prior to completely filling the pouch. For example, in order to target a fill volume of approximately 40 mL, fill to the level indicated by the arrows in Figure 1. Ensure the pouch is hanging vertically.
• The tube leading from the Y-junction to the sample pouch contains an additional volume of approximately 2 mL.

Precautions:

• Do not elevate or squeeze the sample pouch as this could cause blood to backflow from the sample pouch into the collection system.
• Once the sample pouch is filled to desired volume, complete steps 11–19 within approximately 4 minutes to avoid possible clot formation in the tubing and/or sample pouch.

11. Close the blue clamp on tubing between the Y-junction and the sample pouch.

12. Break the in-line cannula below the Y-junction in the donor tubing to the primary container allowing blood collection to proceed. To completely break the in-line cannula, grasp with both hands. Snap it at a 90° angle in one direction, and then bend it at a 90° angle in the opposite direction. Ensure the in-line cannula is completely broken and that the blood flows freely to the primary container.

Precaution: Failure to break the in-line cannula completely may result in restricted blood flow.

13. Mix blood and anticoagulant in primary container immediately, at several intervals during collection and immediately after collection.

14. Following blood center procedures, hermetically seal the tubing between the sampling site and the Y-junction to maintain sterility of the blood collection system prior to removing blood samples.

Warning:

• Do not proceed with the remaining steps until the tubing leading to the sample pouch is hermetically sealed between the sampling site and the Y-junction. To maintain the whole blood collection container as a closed system, the tubing between the sample pouch and Y-junction must be hermetically sealed prior to inserting the access device into the sampling site. Failure to do so may lead to contamination of the whole blood collection.

15. To collect samples, insert the access device by pushing firmly into the sampling site until the membrane seal is penetrated.

Note: If the access device is assembled such that the outer barrel is screwed onto the Luer, make sure to rotate clockwise upon insertion to avoid barrel detaching from Luer.

16. Open the cap on the access device (if applicable). Hold access device so that the sample pouch hangs down.

17. Directly align the vacuum sample tube with the internal needle in the access device. Insert vacuum sample tube into device.

18. Allow vacuum sample tube to fill with blood then remove from the access device.

19. Repeat steps 17 and 18 until the desired number of vacuum sample tubes have been filled.

Notes:

• If the access device needs to be replaced, clamp the tubing between the sampling site and the sample pouch. Then, grasp base of sampling site with one hand and pull the access device out with the other hand. Firmly insert the new access device. Remove clamp and continue sampling.
• If the access device is assembled such that the outer barrel is screwed onto the Luer, make sure to rotate clockwise upon removal to avoid barrel detaching from Luer.
• The access device can only be replaced one time. Precaution: When replacing access device, be careful to avoid contact with any blood droplets on the Luer or sampling site. Discard used access device appropriately.

20. Collect only 450 ± 45 mL of blood into the elongated primary container.

Precaution: The primary container of this blood collection system is larger than conventional primary containers and will not appear as full as smaller containers when 450 mL of blood has been collected. The amount of blood collected should be determined by weight for collection of 450 mL of blood.

Precaution: Once the desired blood volume is collected, complete steps 21–24 within approximately 4 minutes to avoid possible clot formation in the tubing.

21. Release pressure on the donor’s arm. If appropriate, apply clamp to donor tubing between the needle and the Y-junction.

22. Hermetically seal donor tubing near in-line cannula on side leading to the primary container.

23. Withdrawal of Needle (see Figure 3)

Precaution: The needle guard must be held stationary while the needle is withdrawn into it.

a) Place folded sterile gauze over puncture site and hold in place with finger tip without exerting pressure.
b) Hold sides of needle guard near the front, between the index finger and thumb. Pull the hub back smoothly until the needle is completely enclosed and securely locked into the needle guard.
c) Confirm the needle is completely enclosed and securely locked into the needle guard.

24. Strip blood from donor tubing into primary container, mix and allow the tubing to refill; repeat once.

25. Seal at X marks on donor tubing to provide numbered aliquots of anticoagulated blood for typing or crossmatching.

Note: Step 26 may be performed prior to step 24 or 25 if desired.

26. Remove and discard the Sample Diversion System and needle in the needle guard into an appropriate biohazardous waste container following established procedures.

27. For component preparation, prior to centrifugation, the excess material at bottom of the elongated primary container should be rolled over as follows:

• To perform bottom rolling, invert primary container (Figure 4A).
• With ports down, roll over excess container material (Figure 4B) and secure with tape (Figure 4C).
• Place the rolled primary container in an upright position (ports up) on top of secondary containers in centrifuge cup (Figure 4D).

28. At the appropriate time, prepare the Blood-Pack unit for centrifugation by thoroughly mixing the primary container end over end, then load the unit in a centrifuge cup per the instructions on page 4.

29. Gently remove the (bottom-rolled) elongated primary container from centrifuge cup. Using care to ensure that bottom fold area is supported, place the container in the plasma extractor.

30. Express plasma into empty Transfer Pack container by releasing pressure plate and opening closure in tubing of primary container. All visible (platelet rich) plasma should be removed if cells are to be frozen subsequently.

31. When desired amount of plasma has been removed, clamp tubing between Y and plasma container, remove tape, and unfold unit.

32. Seal transfer tubing in three places between the Y-connectors. Cut middle seal being careful to avoid fluid splatter.

33. For further processing with multiple Blood-Pack units, use standard component processing and storage techniques.

For Liquid Red Cell Storage:

34. Store suspended CPDA-1 Whole Blood/Red Blood Cells between 1 and 6°C and

infuse within 35 days of collection.

For Frozen Red Cell Storage:

Precaution: Freeze within 6 days of collection. Use aseptic technique during red cell glycerolization.

35. If remaining Red Blood Cells are intended for frozen storage in the elongated primary container, the hematocrit should be between 75 and 80% and one empty container should be left attached to the primary for glycerol removal.

36. Supplies

A) Glycerolyte 57 Solution, 500 mL (Code 4A7833)
B) Plasma Transfer Set (Code 4C2243 or similar)
C) Sterile Filtered Airway Needle (if required)
D) Labels for elongated primary freezing pack and cardboard storage container
E) 1 heat-sealable 8" x 12" plastic bag
F) Corrugated 7" x 5" x 1-1/2" cardboard protective container
G) 70% isopropyl alcohol swabs
H) Waterproof tape
I) Hand sealer clips (Code 4R4418)
J) Agitator
K) Plasma Extractor (Code 4R4414)

37. Allow glycerol solution and red cells to warm to 22–30°C prior to adding solution to red cells. Process cells within 4 hours after removal from refrigeration.

38. Remove all but one numbered tubing segment. Heat seal the remaining segment as close to the container as possible. Leave the segment attached to the container.

39. Weigh the unit of red cell concentrate and subtract the tare weight (approx. 72 grams for the elongated primary container and integrally attached Transfer Pack container). The net weight of the red cells should not exceed 330 grams.

40. Place the red cell concentrate on a platform agitator.

41. Remove the metal tab from the top of the glycerol solution bottle, disinfect the stopper with 70% isopropyl alcohol and aseptically insert one of the plasma transfer set couplers into the bottle outlet port. Close roller clamp on plasma transfer set.

42. Insert the filtered airway needle into the bottle vent port.

43. Invert the bottle and suspend it 18 inches above the level of the primary bag on the agitator.

44. Aseptically connect the remaining transfer set connector to the delivery tube leading from the elongated primary container.

45. Glycerol solution should be added to cells based on cell volume and in three steps. Refer to Table 1.

46. Adjust platform agitator to 180 oscillations/minute. Occlude tubing between elongated primary collection container and empty Transfer Pack container by folding tubing and placing a hand sealer clip over fold (do not crimp) to prevent flow of solution into Transfer Pack container.

47. Add 50 mL of glycerol solution to the red cells while the cells are being agitated.

48. Turn off agitator and allow equilibration for 5 minutes.

49. Restart agitator; add 50 mL of glycerol solution to cells.

50. Turn off agitator and allow equilibration for 2 minutes.

51. Remove red cells from agitator.

52. Refer to Table 1 to determine remaining volume of glycerol solution to be added to red cells. Use continuous, vigorous manual agitation during solution addition.

53. Seal tubing proximal to the delivery tube assembly. Ensure that the Transfer Pack container remains integrally attached to the primary collection bag. Discard the glycerol bottle, connector tubing, and delivery tube assembly.

54. Centrifuge the glycerolized red cells at 1250 x g for 10 minutes.

55. Suspend primary container in plasma extractor, remove hand sealer clip, and express all visible supernatant glycerol from the red cell container into the Transfer Pack container.

56. Seal the tubing 2 inches from the red cell container, separate tubing and discard the Transfer Pack container containing the supernatant glycerol solution.

57. Appropriately label product (Figure 5A).

58. Fold over the top portion of the primary bag approximately 2 inches (Figure 5B), place the unit into the 8" x 12" plastic overwrap (Figure 5C) and seal across the top using an impulse sealer so that there is as little trapped air as possible. Make sure that the ports and tubing segments are folded beneath the unit so that they are protected from breakage when frozen.

59. Place the glycerolized red cells and overwrap into the cardboard box (Figure 5D). Close the box and seal the flaps with tape. Label the box, and place in the bottom of a -80°C freezer. To facilitate freezing, do not stack units. After 24 hours, the

frozen units can be stacked and/or stored in other -80°C freezers.

60. After storage, thaw and deglycerolize red cells according to standard institutional procedure.

61. Infuse deglycerolized cells within 24 hours after processing.

References

Freezing in the Primary Polyvinylchloride Plastic Collection Bag: A new system for freezing nonrejuvenated and rejuvenated Red Blood Cells. C.R. Valeri, D.A. Valeri, J. Anastasi, J.J. Vecchione, R.C. Dennis, and C.P. Emerson. Transfusion 1981; 21:138-149.

Store at Controlled Room Temperature. Protect from freezing. Avoid excessive heat. Definition of “Controlled Room Temperature”:

“A temperature maintained thermostatically that encompasses the usual and customary working environment of 20° to 25°C (68° to 77°F); that results in a mean kinetic temperature calculated to be not more than 25°C; and that allows for excursions between 15°C and 30°C (59° and 86°F) that are experienced in pharmacies, hospitals, and warehouses. Provided the mean kinetic temperature remains in the allowed range, transient spikes up to 40°C are permitted as long as they do not exceed 24 hours ... The mean kinetic temperature is a calculated value that may be used as an isothermal storage temperature that simulates the non isothermal effects of storage temperature variations.”

Reference: United States Pharmacopeia, General Notices. United States Pharmacopeial

Convention, Inc. 12601 Twinbrook Parkway, Rockville, MD.

^1Van der Meer, P.F., & de Korte, D. “Increase of blood donation speed by optimizing the needle-totubing connection: an application of donation software.” Vox Sanguinis 2009, 97: 21-25.

Sorvall is a trademark of Thermo Fisher Scientific LLC.

© 2019 Fresenius Kabi AG. All rights reserved.

Manufacturer

Fresenius Kabi AG

61346 Bad Homburg / Germany

www.fresenius-kabi.com

1-800-933-6925

47-23-13-769 REV: A

PACKAGE/LABEL DISPLAY PANEL

Code 4R1250 3 Units

Fenwal Blood-Pack Units Quadruple

Anticoagulant Citrate Phosphate Dextrose Adenine Solution, USP (CPDA-1) with Elongated Primary Container

For Collection of 450 mL Blood and Optional Freezing of Red Blood Cells in the Primary Container Sample Diversion System, 16 ga. Ultra Thin Wall Fenwal HighFlo Needle

Rx only

Each unit consists of an elongated primary container with delivery tube assembly and with 63 mL of CPDA-1 solution containing 2 g Dextrose (monohydrate) USP, 1.66 g Sodium Citrate (dihydrate) USP, 188 mg Citric Acid (anhydrous) USP, 140 mg Monobasic Sodium Phosphate (monohydrate) USP and 17.3 mg Adenine USP, pH may have been adjusted with sodium hydroxide; three empty 400 mL Plastic Transfer-Pack containers.

Sterile, non-pyrogenic fluid path
See instructions for use.

Single use only.

Store at Controlled Room Temperature (refer to direction insert). Protect from freezing. Avoid excessive heat.

- Open pouch by tearing across at notch.
- Direct handling of product surfaces prior to extended storage in the foil pouch, may result in mold growth.
- Unused units in open foil pouch may be kept up to 60 days by folding and securing open end of foil pouch to prevent possible loss of moisture, provided:
I. Units are not removed from foil pouch, or
II. Unused units removed from foil pouch are returned to the foil pouch within 12 hours. Units may be removed from the pouch and returned only once.
- Units removed from the foil pouch (that are not returned to the pouch within 12 hours) must be used within 4 days (96 hours). Units out of the foil pouch for longer than 96 hours must be discarded.

Manufacturer

Fresenius Kabi AG

61346 Bad Homburg / Germany

www.fresenius-kabi.com

Made in US

47-28-13-770 REV: A